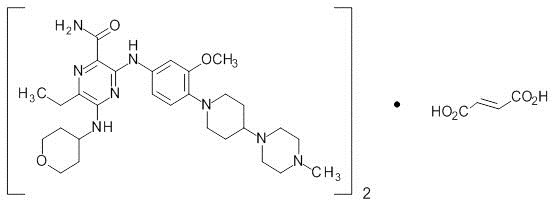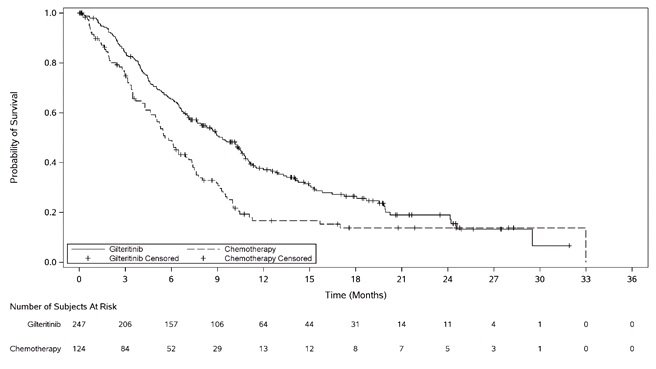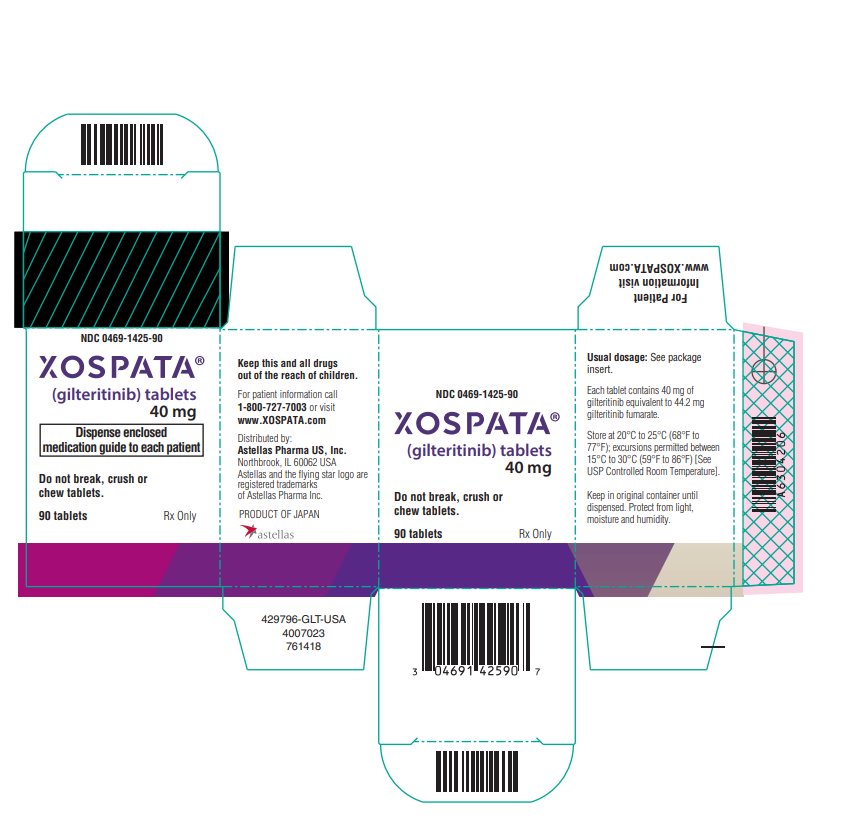 DRUG LABEL: Xospata
NDC: 0469-1425 | Form: TABLET
Manufacturer: Astellas Pharma US, Inc.
Category: prescription | Type: HUMAN PRESCRIPTION DRUG LABEL
Date: 20220101

ACTIVE INGREDIENTS: GILTERITINIB FUMARATE 40 mg/1 1
INACTIVE INGREDIENTS: MANNITOL; HYDROXYPROPYL CELLULOSE, UNSPECIFIED; LOW-SUBSTITUTED HYDROXYPROPYL CELLULOSE, UNSPECIFIED; MAGNESIUM STEARATE; HYPROMELLOSE, UNSPECIFIED; TALC; POLYETHYLENE GLYCOL, UNSPECIFIED; TITANIUM DIOXIDE; FERRIC OXIDE RED

HIGHLIGHTS OF PRESCRIBING INFORMATION

These highlights do not include all the information needed to use XOSPATA safely and effectively. See full prescribing information for XOSPATA.
XOSPATA® (gilteritinib) tablets, for oral use
Initial U.S. Approval: 2018

WARNING: DIFFERENTIATION SYNDROME

See full prescribing information for complete boxed warning.

Patients treated with XOSPATA have experienced symptoms of differentiation syndrome, which can be fatal if not treated. If differentiation syndrome is suspected, initiate corticosteroid therapy and hemodynamic monitoring until symptom resolution. (5.1, 6.1)

1 INDICATIONS AND USAGE

XOSPATA is a kinase inhibitor indicated for the treatment of adult patients who have relapsed or refractory acute myeloid leukemia (AML) with a FLT3 mutation as detected by an FDA-approved test. (1.1)

2 DOSAGE AND ADMINISTRATION

120 mg orally once daily. (2.2)

3 DOSAGE FORMS AND STRENGTHS

Tablets: 40 mg. (3)

4 CONTRAINDICATIONS

Hypersensitivity to gilteritinib or any of the excipients. Anaphylactic reactions have been observed in clinical trials. (4, 6.1)

5 WARNINGS AND PRECAUTIONS

- Posterior reversible encephalopathy syndrome (PRES): Discontinue XOSPATA in patients who develop PRES. (2.3, 5.2, 6.1)
- Prolonged QT Interval: Interrupt and reduce XOSPATA dosage in patients who have a QTcF >500 msec. Correct hypokalemia or hypomagnesemia prior to and during XOSPATA administration. (2.3, 5.3, 12.2, 6.1)
- Pancreatitis: Interrupt and reduce the dose in patients who develop pancreatitis. (2.3, 5.4)
- Embryo-Fetal Toxicity: XOSPATA can cause fetal harm when administered to a pregnant woman. Advise of the potential risk to a fetus and to use effective contraception. (5.5, 8.1, 8.3)

6 ADVERSE REACTIONS

The most common adverse reactions (≥20%) are transaminase increased, myalgia/arthralgia, fatigue/malaise, fever, mucositis, edema, rash, noninfectious diarrhea, dyspnea, nausea, cough, constipation, eye disorders, headache, dizziness, hypotension, vomiting, and renal impairment. (6.1)

To report SUSPECTED ADVERSE REACTIONS, contact Astellas Pharma US, Inc. at 1-800-727-7003 or FDA at 1-800-FDA-1088 or www.fda.gov/medwatch.

7 DRUG INTERACTIONS

- Combined P-gp and Strong CYP3A Inducers: Avoid concomitant use. (7.1)
- Strong CYP3A Inhibitors: Consider alternative therapies. If the concomitant use of strong CYP3A inhibitors cannot be avoided, monitor patients more frequently for XOSPATA adverse reactions. (2.3, 7.1)
- P-gp, BCRP, OCT1 Substrates: Decrease the dose of the substrates when coadministered with gilteritinib and as clinically indicated. (7.2)

8 USE IN SPECIFIC POPULATIONS

Lactation: Advise women not to breastfeed. (8.2)

FULL PRESCRIBING INFORMATION

WARNING: DIFFERENTIATION SYNDROME

Patients treated with XOSPATA have experienced symptoms of differentiation syndrome, which can be fatal or life-threatening if not treated. Symptoms may include fever, dyspnea, hypoxia, pulmonary infiltrates, pleural or pericardial effusions, rapid weight gain or peripheral edema, hypotension, or renal dysfunction. If differentiation syndrome is suspected, initiate corticosteroid therapy and hemodynamic monitoring until symptom resolution [see Warnings and Precautions (5.1) and Adverse Reactions (6.1)].

1 INDICATIONS AND USAGE

1.1 Relapsed or Refractory Acute Myeloid Leukemia

XOSPATA is indicated for the treatment of adult patients who have relapsed or refractory acute myeloid leukemia (AML) with a FMS-like tyrosine kinase 3 (FLT3) mutation as detected by an FDA-approved test.

2 DOSAGE AND ADMINISTRATION

2.1 Patient Selection

Select patients for the treatment of AML with XOSPATA based on the presence of FLT3 mutations in the blood or bone marrow [see Clinical Studies (14)]. Information on FDA-approved tests for the detection of a FLT3 mutation in AML is available at http://www.fda.gov/CompanionDiagnostics.

2.2 Recommended Dosage

The recommended starting dose of XOSPATA is 120 mg orally once daily with or without food. Response may be delayed. In the absence of disease progression or unacceptable toxicity, treatment for a minimum of 6 months is recommended to allow time for a clinical response.

Do not break or crush XOSPATA tablets. Administer XOSPATA tablets orally about the same time each day. If a dose of XOSPATA is missed or not taken at the usual time, administer the dose as soon as possible on the same day, and at least 12 hours prior to the next scheduled dose. Return to the normal schedule the following day. Do not administer 2 doses within 12 hours.

2.3 Dosage Modifications

Assess blood counts and blood chemistries, including creatine phosphokinase, prior to the initiation of XOSPATA, at least once weekly for the first month, once every other week for the second month, and once monthly for the duration of therapy. Perform electrocardiogram (ECG) prior to initiation of treatment with gilteritinib, on days 8 and 15 of cycle 1, and prior to the start of the next two subsequent cycles.

Interrupt dosing or reduce dose for toxicities as per Table 1.

Table 1: Dosage Modifications for XOSPATA-Related Toxicities [Grade 1 is mild, Grade 2 is moderate, Grade 3 is serious, Grade 4 is life-threatening.]
Adverse Reaction | Recommended Action
Differentiation Syndrome | - If differentiation syndrome is suspected, administer systemic corticosteroids and initiate hemodynamic monitoring until symptom resolution and for a minimum of 3 days [see Warnings and Precautions (5.1)]. - Interrupt XOSPATA if severe signs and/or symptoms persist for more than 48 hours after initiation of corticosteroids [see Warnings and Precautions (5.1)]. - Resume XOSPATA when signs and symptoms improve to Grade 2 or lower.
Posterior Reversible Encephalopathy Syndrome | - Discontinue XOSPATA.
QTc interval greater than 500 msec | - Interrupt XOSPATA. - Resume XOSPATA at 80 mg when QTc interval returns to within 30 msec of baseline or less than or equal to 480 msec.
QTc interval increased by >30 msec on ECG on day 8 of cycle 1 | - Confirm with ECG on day 9. - If confirmed, consider dose reduction to 80 mg.
Pancreatitis | - Interrupt XOSPATA until pancreatitis is resolved. - Resume XOSPATA at 80 mg.
Other Grade 3 or higher toxicity considered related to treatment. | - Interrupt XOSPATA until toxicity resolves or improves to Grade 1. - Resume XOSPATA at 80 mg.

3 DOSAGE FORMS AND STRENGTHS

Tablets: 40 mg as light yellow, round-shaped, film-coated tablets debossed with the Astellas logo and ‘235’ on the same side.

4 CONTRAINDICATIONS

XOSPATA is contraindicated in patients with hypersensitivity to gilteritinib or any of the excipients. Anaphylactic reactions have been observed in clinical trials [see Adverse Reactions (6) and Description (11)].

5 WARNINGS AND PRECAUTIONS

5.1 Differentiation Syndrome

Of 319 patients treated with XOSPATA in the clinical trials, 3% experienced differentiation syndrome. Differentiation syndrome is associated with rapid proliferation and differentiation of myeloid cells and may be life-threatening or fatal if not treated. Symptoms and other clinical findings of differentiation syndrome in patients treated with XOSPATA included fever, dyspnea, pleural effusion, pericardial effusion, pulmonary edema, hypotension, rapid weight gain, peripheral edema, rash, and renal dysfunction. Some cases had concomitant acute febrile neutrophilic dermatosis. Differentiation syndrome occurred as early as 1 day and up to 82 days after XOSPATA initiation and has been observed with or without concomitant leukocytosis. Of the 11 patients who experienced differentiation syndrome, 9 (82%) recovered after treatment or after dose interruption of XOSPATA.

If differentiation syndrome is suspected, initiate dexamethasone 10 mg IV every 12 hours (or an equivalent dose of an alternative oral or IV corticosteroid) and hemodynamic monitoring until improvement. Taper corticosteroids after resolution of symptoms and administer corticosteroids for a minimum of 3 days. Symptoms of differentiation syndrome may recur with premature discontinuation of corticosteroid treatment. If severe signs and/or symptoms persist for more than 48 hours after initiation of corticosteroids, interrupt XOSPATA until signs and symptoms are no longer severe [see Dosage and Administration (2.3)].

5.2 Posterior Reversible Encephalopathy Syndrome

Of 319 patients treated with XOSPATA in the clinical trials, 1% experienced posterior reversible encephalopathy syndrome (PRES) with symptoms including seizure and altered mental status. Symptoms have resolved after discontinuation of XOSPATA. A diagnosis of PRES requires confirmation by brain imaging, preferably magnetic resonance imaging (MRI). Discontinue XOSPATA in patients who develop PRES [see Dosage and Administration (2.3) and Adverse Reactions (6.1)].

5.3 Prolonged QT Interval

XOSPATA has been associated with prolonged cardiac ventricular repolarization (QT interval). Of the 317 patients with a post-baseline QTc measurement on treatment with XOSPATA in the clinical trial, 1% were found to have a QTc interval greater than 500 msec and 7% of patients had an increase from baseline QTc greater than 60 msec. Perform electrocardiogram (ECG) prior to initiation of treatment with gilteritinib, on days 8 and 15 of cycle 1, and prior to the start of the next two subsequent cycles. Interrupt and reduce XOSPATA dosage in patients who have a QTcF >500 msec [see Dosage and Administration (2.3), Adverse Reactions (6.1) and Clinical Pharmacology (12.2)].

Hypokalemia or hypomagnesemia may increase the QT prolongation risk. Correct hypokalemia or hypomagnesemia prior to and during XOSPATA administration.

5.4 Pancreatitis

Of 319 patients treated with XOSPATA in the clinical trials, 4% experienced pancreatitis. Evaluate patients who develop signs and symptoms of pancreatitis. Interrupt and reduce the dose of XOSPATA in patients who develop pancreatitis [see Dosage and Administration (2.3)].

5.5 Embryo-Fetal Toxicity

Based on findings in animals and its mechanism of action, XOSPATA can cause embryo-fetal harm when administered to a pregnant woman. In animal reproduction studies, administration of gilteritinib to pregnant rats during organogenesis caused embryo-fetal lethality, suppressed fetal growth and teratogenicity at maternal exposures (AUC24) approximately 0.4 times the AUC24 in patients receiving the recommended dose. Advise females of reproductive potential to use effective contraception during treatment with XOSPATA and for 6 months after the last dose of XOSPATA. Advise males with female partners of reproductive potential to use effective contraception during treatment with XOSPATA and for 4 months after the last dose of XOSPATA. Pregnant women, patients becoming pregnant while receiving XOSPATA or male patients with pregnant female partners should be apprised of the potential risk to the fetus [see Use in Specific Populations (8.1, 8.3) and Clinical Pharmacology (12.1)].

6 ADVERSE REACTIONS

The following clinically significant adverse reactions are described elsewhere in the labeling:

- Differentiation syndrome [see Boxed Warning and Warnings and Precautions (5.1)]
- Posterior reversible encephalopathy syndrome [see Warnings and Precautions (5.2)]
- Prolonged QT interval [see Warnings and Precautions (5.3)]
- Pancreatitis [see Warnings and Precautions (5.4)]

6.1 Clinical Trials Experience

Because clinical trials are conducted under widely varying conditions, adverse reaction rates observed in the clinical trials of a drug cannot be directly compared to rates in the clinical trials of another drug and may not reflect the rates observed in practice.

The safety profile of XOSPATA is based on 319 patients with relapsed or refractory AML treated with gilteritinib 120 mg daily in three clinical trials. The median duration of exposure to XOSPATA was 3.6 months (range 0.1 to 43.4 months).

Fatal adverse reactions occurred in 2% of patients receiving XOSPATA. These included cardiac arrest (1%) and one case each of differentiation syndrome and pancreatitis. The most frequent (≥5%) nonhematological serious adverse reactions reported in patients were fever (13%), dyspnea (9%), renal impairment (8%), transaminase increased (6%) and noninfectious diarrhea (5%).

Of the 319 patients, 91 (29%) required a dose interruption due to an adverse reaction; the most common adverse reactions leading to dose interruption were aspartate aminotransferase increased (6%), alanine aminotransferase increased (6%) and fever (4%). Twenty patients (6%) required a dose reduction due to an adverse reaction. Twenty-two (7%) discontinued XOSPATA treatment permanently due to an adverse reaction. The most common (>1%) adverse reactions leading to discontinuation were aspartate aminotransferase increased (2%) and alanine aminotransferase increased (2%).

Overall, for the 319 patients, the most frequent (≥10%) all-grade nonhematological adverse reactions reported in patients were transaminase increased (51%), myalgia/arthralgia (50%), fatigue/malaise (44%), fever (41%), mucositis (41%), edema (40%), rash (36%), noninfectious diarrhea (35%), dyspnea (35%), nausea (30%), cough (28%), constipation (28%), eye disorders (25%), headache (24%), dizziness (22%), hypotension (22%), vomiting (21%), renal impairment (21%), abdominal pain (18%), neuropathy (18%), insomnia (15%) and dysgeusia (11%). The most frequent (≥5%) grade ≥3 nonhematological adverse reactions reported in patients were transaminase increased (21%), dyspnea (12%), hypotension (7%), mucositis (7%), myalgia/arthralgia (7%), and fatigue/malaise (6%). Shifts to grades 3-4 nonhematologic laboratory abnormalities included phosphate decreased 42/309 (14%), alanine aminotransferase increased 41/317 (13%), sodium decreased 37/314 (12%), aspartate aminotransferase increased 33/317 (10%), calcium decreased 19/312 (6%), creatine kinase increased 20/317 (6%), triglycerides increased 18/310 (6%), creatinine increased 10/316 (3%), and alkaline phosphatase increased 5/317 (2%).

Adverse reactions reported in the first 30 days of therapy on the ADMIRAL Study [see Clinical Studies (14)] are shown in Tables 2 and 3, according to whether patients were preselected for high intensity or low intensity chemotherapy.

Table 2: Adverse Reactions Reported in ≥10% (Any Grade) or ≥5% (Grade 3-5) [Grade 3-5 includes serious, life-threatening and fatal adverse reactions] of Patients with Relapsed or Refractory AML in the Pre-selected High Intensity Chemotherapy Subgroup in the First 30 Days of the ADMIRAL Trial
Adverse Reaction | Any Grade; n (%) |  | Grade ≥3; n (%)
Adverse Reaction | XOSPATA; (120 mg daily); n=149 | Chemotherapy n=68 | XOSPATA; (120 mg daily); n=149 | Chemotherapy n=68
Musculoskeletal and connective tissue disorders
Myalgia/arthralgia [Grouped terms: arthralgia, back pain, bone pain, flank pain, limb discomfort, medial tibial stress syndrome, myalgia, muscle twitching, musculoskeletal discomfort, musculoskeletal pain, muscle spasms, neck pain, non-cardiac chest pain, pain and pain in extremity] | 56 (38) | 20 (29) | 1 (1) | 3 (4)
Investigations
Transaminase increased [Grouped terms: aspartate aminotransferase increased, alanine aminotransferase increased, blood alkaline phosphatase increased, gamma-glutamyltransferase increased, hepatic enzyme increased, hepatic function abnormal, hepatoxicity, liver function test increased and transaminases increased] | 46 (31) | 11 (16) | 15 (10) | 5 (7)
General disorders and administration site conditions
Fatigue/malaise [Grouped terms: asthenia, fatigue, lethargy and malaise] | 36 (24) | 9 (13) | 1 (1) | 2 (3)
Fever | 25 (17) | 21 (31) | 2 (1) | 4 (6)
Edema [Grouped terms: edema, edema peripheral, face edema, fluid overload, generalized edema, hypervolemia, localized edema, periorbital edema and swelling face] | 20 (13) | 13 (19) | 0 | 0
Gastrointestinal disorders
Constipation | 29 (20) | 10 (15) | 0 | 0
Mucositis [Grouped terms: aphthous ulcer, colitis, enteritis, esophageal pain, gingival pain, large intestinal ulcer, laryngeal inflammation, lip blister, lip ulceration, mouth hemorrhage, mouth ulceration, mucosal inflammation, oral discomfort, oral pain, oropharyngeal pain, proctalgia, stomatitis, swollen tongue, tongue discomfort and tongue ulceration] | 18 (12) | 30 (44) | 0 | 5 (7)
Nausea | 23 (15) | 26 (38) | 0 | 0
Abdominal pain [Grouped terms: abdominal discomfort, abdominal pain, abdominal pain lower, abdominal pain upper and gastrointestinal pain] | 16 (11) | 16 (24) | 0 | 0
Blood and lymphatic system disorder
Febrile neutropenia | 26 (17) | 30 (44) | 26 (17) | 30 (44)
Skin and subcutaneous tissue disorders
Rash [Grouped terms: acne, dermatitis bullous, dermatitis contact, drug eruption, eczema asteatotic, erythema, hyperkeratosis, lichenoid keratosis, palmar-plantar erythrodysesthesia syndrome, rash, rash maculo-papular, rash papular, skin exfoliation, skin lesion and skin hyperpigmentation] | 23 (15) | 21 (31) | 1 (1) | 2 (3)
Respiratory, thoracic and mediastinal disorders
Dyspnea [Grouped terms: acute respiratory distress syndrome, dyspnea, dyspnea exertional, hypoxia, pulmonary edema, respiratory failure, tachypnea and wheezing] | 20 (13) | 9 (13) | 1 (1) | 6 (9)
Cough | 18 (12) | 5 (7) | 1 (1) | 0
Nervous system disorders
Neuropathy [Grouped terms: hyperesthesia, hypoesthesia, neuralgia, neuropathy peripheral, peripheral sensory neuropathy and paresthesia] | 19 (13) | 0 | 0 | 0
Dizziness [Grouped terms: coordination abnormal and dizziness] | 17 (11) | 2 (3) | 0 | 0
Headache | 17 (11) | 12 (18) | 0 | 0

Table 3: Adverse Reactions Reported in ≥10% (Any Grade) or ≥5% (Grade 3-5) [Grade 3-5 includes serious, life-threatening and fatal adverse reactions] of Patients with Relapsed or Refractory AML in the Pre-selected Low Intensity Chemotherapy Subgroup in the First 30 Days of the ADMIRAL Trial
Adverse Reaction | Any Grade; n (%) |  | Grade ≥3; n (%)
Adverse Reaction | XOSPATA; (120 mg daily); n=97 | Chemotherapy n=41 | XOSPATA; (120 mg daily); n=97 | Chemotherapy n=41
Investigations
Transaminase increased [Grouped terms: aspartate aminotransferase increased, alanine aminotransferase increased, blood alkaline phosphatase increased and transaminases increased] | 35 (36) | 6 (15) | 9 (9) | 1 (2)
Blood and lymphatic system disorder
Febrile neutropenia | 26 (27) | 5 (12) | 25 (26) | 5 (12)
Musculoskeletal and connective tissue disorders
Myalgia/arthralgia [Grouped terms: arthralgia, arthritis, back pain, limb discomfort, myalgia, muscle contracture, muscle spasms, myositis, non-cardiac chest pain, pain, pain in extremity and polyarthritis] | 21 (22) | 7 (17) | 2 (2) | 0
General disorders and administration site conditions
Fatigue/malaise [Grouped terms: asthenia, fatigue and malaise] | 20 (21) | 9 (22) | 4 (4) | 1 (2)
Edema [Grouped terms: edema, face edema, localized edema, edema peripheral, peripheral swelling, periorbital edema, scrotal edema and swelling face] | 19 (20) | 5 (12) | 1 (1) | 0
Fever | 11 (11) | 7 (17) | 0 | 0
Gastrointestinal disorders
Mucositis [Grouped terms: colitis, mouth hemorrhage, mouth ulceration, mucosal inflammation, oropharyngeal pain, proctalgia, stomatitis, tongue discomfort and tongue ulceration] | 19 (20) | 7 (17) | 1 (1) | 1 (2)
Constipation | 13 (13) | 5 (12) | 1 (1) | 0
Diarrhea | 12 (12) | 2 (5) | 0 | 0
Nausea | 10 (10) | 7 (17) | 0 | 0
Respiratory, thoracic and mediastinal disorders
Dyspnea [Grouped terms: acute respiratory failure, dyspnea, hypoxia and respiratory failure] | 11 (11) | 2 (5) | 3 (3) | 2 (5)
Skin and subcutaneous tissue disorders
Rash [Grouped terms: dermatitis acneiform, dermatitis bullous, dermatitis exfoliative, erythema, rash, rash maculo-papular, rash papular, rosacea and skin ulcer] | 10 (10) | 2 (5) | 2 (2) | 0

Other clinically significant adverse reactions occurring in ≤10% of patients included: electrocardiogram QT prolonged (9%), hypersensitivity* (8%), pancreatitis* (5%), cardiac failure* (4%), pericardial effusion (4%), acute febrile neutrophilic dermatosis (3%), differentiation syndrome (3%), pericarditis/myocarditis* (2%), large intestine perforation (1%), and posterior reversible encephalopathy syndrome (1%).

*Grouped terms: cardiac failure (cardiac failure, cardiac failure congestive, cardiomegaly, cardiomyopathy, chronic left ventricular failure, and ejection fraction decreased), hypersensitivity (anaphylactic reaction, angioedema, dermatitis allergic, drug hypersensitivity, erythema multiforme, hypersensitivity, and urticaria), pancreatitis (amylase increased, lipase increased, pancreatitis, pancreatitis acute), pericarditis/myocarditis (myocarditis, pericardial hemorrhage, pericardial rub, and pericarditis).

Selected post-baseline laboratory values that were observed in patients with relapsed or refractory AML are shown in Table 4.

Table 4: Shifts to Grade 3-4 Laboratory Abnormalities in Patients with Relapsed or Refractory AML by Pre-selected High Intensity and Low Intensity Chemotherapy in the First 30 Days of the ADMIRAL Trial
 | Pre-selected High Intensity Chemotherapy Subgroup |  | Pre-selected Low Intensity Chemotherapy Subgroup
 | XOSPATA; (120 mg daily) | Chemotherapy | XOSPATA; (120 mg daily) | Chemotherapy
Alanine aminotransferase increased | 7/149 (5%) | 1/66 (2%) | 7/95 (7%) | 1/41 (2%)
Alkaline phosphatase increased | 1/149 (1%) | 0 | 0 | 0
Aspartate aminotransferase increased | 8/149 (5%) | 2/65 (3%) | 5/95 (5%) | 0
Calcium decreased | 2/149 (1%) | 3/65 (5%) | 3/94 (3%) | 0
Creatine kinase increased | 1/149 (1%) | 0 | 1/95 (1%) | 0
Phosphatase decreased | 4/144 (3%) | 6/65 (9%) | 4/93 (4%) | 3/38 (8%)
Sodium decreased | 7/148 (5%) | 5/65 (8%) | 6/93 (6%) | 2/41 (5%)
Triglycerides increased | 1/146 (1%) | 0 | 2/94 (2%) | 0

7 DRUG INTERACTIONS

7.1 Effect of Other Drugs on XOSPATA

Combined P-gp and Strong CYP3A Inducers

Concomitant use of XOSPATA with a combined P-gp and strong CYP3A inducer decreases gilteritinib exposure which may decrease XOSPATA efficacy [see Clinical Pharmacology (12.3)]. Avoid concomitant use of XOSPATA with combined P-gp and strong CYP3A inducers.

Strong CYP3A Inhibitors

Concomitant use of XOSPATA with a strong CYP3A inhibitor increases gilteritinib exposure [see Clinical Pharmacology (12.3)]. Consider alternative therapies that are not strong CYP3A inhibitors. If the concomitant use of these inhibitors is considered essential for the care of the patient, monitor patient more frequently for XOSPATA adverse reactions. Interrupt and reduce XOSPATA dosage in patients with serious or life-threatening toxicity [see Dosage and Administration (2.3)].

7.2 Effect of XOSPATA on Other Drugs

Drugs that Target 5HT2B Receptor or Sigma Nonspecific Receptor

Concomitant use of gilteritinib may reduce the effects of drugs that target the 5HT2B receptor or the sigma nonspecific receptor (e.g., escitalopram, fluoxetine, sertraline). Avoid concomitant use of these drugs with XOSPATA unless their use is considered essential for the care of the patient [see Clinical Pharmacology (12.3)].

P-gp, BCRP, and OCT1 Substrates

Based on in vitro data, gilteritinib is a P-gp, breast cancer resistant protein (BCRP), and organic cation transporter 1 (OCT1) inhibitor. Coadministration of gilteritinib may increase the exposure of P-gp, BCRP, and OCT1 substrates, which may increase the incidence and severity of adverse reactions of these substrates [see Clinical Pharmacology (12.3)].

For P-gp, BCRP, or OCT1 substrates where small concentration changes may lead to serious adverse reactions, decrease the dose or modify the dosing frequency of such substrate and monitor for adverse reactions as recommended in the respective prescribing information.

8 USE IN SPECIFIC POPULATIONS

8.1 Pregnancy

Risk Summary

Based on findings from animal studies (see Data) and its mechanism of action, XOSPATA can cause fetal harm when administered to a pregnant woman [see Clinical Pharmacology (12.1)].

There are no available data on XOSPATA use in pregnant women to inform a drug-associated risk of adverse developmental outcomes. In animal reproduction studies, administration of gilteritinib to pregnant rats during organogenesis caused adverse developmental outcomes including embryo-fetal lethality, suppressed fetal growth, and teratogenicity at maternal exposures (AUC24) approximately 0.4 times the AUC24 in patients receiving the recommended dose (see Data). Advise pregnant women of the potential risk to a fetus.

Adverse outcomes in pregnancy occur regardless of the health of the mother or the use of medications. The background risk of major birth defects and miscarriage for the indicated population is unknown. In the U.S. general population, the estimated background risk of major birth defects and miscarriage in clinically recognized pregnancies is 2%-4% and 15%-20%, respectively.

Data

Animal Data

In an embryo-fetal development study in rats, pregnant animals received oral doses of gilteritinib of 0, 0.3, 3, 10, and 30 mg/kg/day during the period of organogenesis. Maternal findings at 30 mg/kg/day (resulting in exposures approximately 0.4 times the AUC24 in patients receiving the recommended dose) included decreased body weight and food consumption. Administration of gilteritinib at the dose of 30 mg/kg/day also resulted in embryo-fetal death (postimplantation loss), decreased fetal body and placental weight, and decreased numbers of ossified sternebrae and sacral and caudal vertebrae, and increased incidence of fetal gross external (anasarca, local edema, exencephaly, cleft lip, cleft palate, short tail, and umbilical hernia), visceral (microphthalmia; atrial and/or ventricular defects; and malformed/absent kidney, and malpositioned adrenal, and ovary), and skeletal (sternoschisis, absent rib, fused rib, fused cervical arch, misaligned cervical vertebra, and absent thoracic vertebra) abnormalities.

Single oral administration of [^14C] gilteritinib to pregnant rats resulted in transfer of radioactivity to the fetus similar to that observed in maternal plasma on day 14 of gestation. In addition, distribution profiles of radioactivity in most maternal tissues and the fetus on day 18 of gestation were similar to that on day 14 of gestation.

8.2 Lactation

Risk Summary

There are no data on the presence of gilteritinib and/or its metabolites in human milk, the effects on the breastfed child, or the effects on milk production. Following administration of radiolabeled gilteritinib to lactating rats, milk concentrations of radioactivity were higher than radioactivity in maternal plasma at 4 and 24 hours post-dose. In animal studies, gilteritinib and/or its metabolite(s) were distributed to the tissues in infant rats via the milk. Because of the potential for serious adverse reactions in a breastfed child, advise a lactating woman not to breastfeed during treatment with XOSPATA and for 2 months after the last dose.

8.3 Females and Males of Reproductive Potential

XOSPATA can cause fetal harm when administered to a pregnant woman [see Use in Specific Populations (8.1)].

Pregnancy testing

Pregnancy testing is recommended for females of reproductive potential within seven days prior to initiating XOSPATA treatment [see Use in Specific Populations (8.1)].

Contraception

Females

Advise females of reproductive potential to use effective contraception during treatment and for 6 months after the last dose of XOSPATA.

Males

Advise males of reproductive potential to use effective contraception during treatment and for 4 months after the last dose of XOSPATA.

8.4 Pediatric Use

Safety and effectiveness in pediatric patients have not been established.

8.5 Geriatric Use

Of the 319 patients in clinical studies of XOSPATA, 43% were age 65 years or older, and 13% were 75 years or older. No overall differences in effectiveness or safety were observed between patients age 65 years or older and younger patients.

11 DESCRIPTION

Gilteritinib is a kinase inhibitor. The chemical name is 2-Pyrazinecarboxamide, 6-ethyl-3-[[3-methoxy-4-[4-(4-methyl-1-piperazinyl)-1-piperidinyl] phenyl] amino]-5-[(tetrahydro-2H-pyran-4-yl) amino]-, (2E)-2-butenedioate (2:1). The molecular weight is 1221.50 and the molecular formula is (C29H44N8O3)2·C4H4O4. The structural formula is:

Gilteritinib fumarate is a light yellow to yellow powder or crystals that is sparingly soluble in water and very slightly soluble in anhydrous ethanol.

XOSPATA (gilteritinib) is provided as a tablet for oral administration. Each tablet contains 40 mg of gilteritinib active ingredient as free base (corresponding to 44.2 mg gilteritinib fumarate). The inactive ingredients are ferric oxide, hydroxypropyl cellulose, hypromellose, low-substituted hydroxypropyl cellulose, mannitol, magnesium stearate, polyethylene glycol, talc, and titanium dioxide.

12 CLINICAL PHARMACOLOGY

12.1 Mechanism of Action

Gilteritinib is a small molecule that inhibits multiple receptor tyrosine kinases, including FMS-like tyrosine kinase 3 (FLT3). Gilteritinib demonstrated the ability to inhibit FLT3 receptor signaling and proliferation in cells exogenously expressing FLT3 including FLT3-ITD, tyrosine kinase domain mutations (TKD) FLT3-D835Y and FLT3-ITD-D835Y, and it induced apoptosis in leukemic cells expressing FLT3-ITD.

12.2 Pharmacodynamics

In patients with relapsed or refractory AML administered gilteritinib 120 mg, substantial (>90%) inhibition of FLT3 phosphorylation was rapid (within 24 hours after first dose) and sustained, as characterized by an ex vivo plasma inhibitory activity (PIA) assay.

Cardiac Electrophysiology

The effect of XOSPATA 120 mg once a day on the QTc interval has been evaluated in patients, which showed an absence of large mean increases (i.e., 20 msec) in the QTc interval.

Of 317 patients with a post-baseline QTc measurement on treatment with gilteritinib at 120 mg in clinical trials, 4 patients (1.3%) experienced a QTcF >500 msec. Additionally, across all doses 2.3% of patients with relapse/refractory AML had a maximum post-baseline QTcF interval >500 msec [see Warnings and Precautions (5.3)].

12.3 Pharmacokinetics

The following pharmacokinetic parameters were observed following administration of gilteritinib 120 mg once daily, unless otherwise specified.

Gilteritinib exposure (Cmax and AUC24) increases proportionally with once daily doses ranging from 20 mg to 450 mg (0.17 to 3.75 times the recommended dosage) in patients with relapsed or refractory AML. Gilteritinib mean (±SD) steady-state Cmax is 374 ng/mL (±190) and AUC24 is 6943 ng•hr/mL (±3221). Steady-state plasma levels are reached within 15 days of dosing with an approximate 10-fold accumulation.

Absorption

The time to maximum gilteritinib concentration (tmax) observed is approximately between 4 and 6 hours post dose in the fasted state.

Effect of Food

In healthy adults administered a single gilteritinib 40 mg dose (0.3 times the recommended dosage), gilteritinib Cmax decreased by 26% and AUC decreased by less than 10% when co-administered with a high-fat meal (approximately 800 to 1,000 total calories with 500 to 600 fat calories, 250 carbohydrate calories, 150 protein calories) compared to a fasted state. Median tmax was delayed 2 hours when gilteritinib was administered with a high-fat meal.

Distribution

The population mean (%CV) estimates of apparent central and peripheral volume of distribution were 1092 L (9.22%) and 1100 L (4.99%), respectively, which may indicate extensive tissue distribution. In vivo, gilteritinib is approximately 94% bound to human plasma proteins. In vitro, gilteritinib is primarily bound to human serum albumin.

Elimination

The estimated half-life of gilteritinib is 113 hours, and the estimated apparent clearance is 14.85 L/h.

Metabolism

Gilteritinib is primarily metabolized via CYP3A4 in vitro. At steady state, the primary metabolites in humans include M17 (formed via N-dealkylation and oxidation), M16 and M10 (both formed via N‑dealkylation). None of these 3 metabolites exceeded 10% of overall parent exposure.

Excretion

After a single radiolabeled dose, gilteritinib is excreted in feces with 64.5% of the total administered dose recovered in feces. Of the total radiolabeled dose of gilteritinib, 16.4% was recovered in urine as unchanged drug and metabolites.

Specific Populations

Age (20-87 years), sex, race, mild (Child-Pugh Class A) or moderate (Child-Pugh Class B) hepatic impairment and mild (creatinine clearance (CLCr) 50-80 mL/min) or moderate (CLCr 30-50 mL/min) renal impairment do not have clinically meaningful effects on the pharmacokinetics of gilteritinib.

The effect of severe hepatic (Child-Pugh Class C) or severe renal impairment (CLCr ≤ 29 mL/min) on gilteritinib pharmacokinetics is unknown.

Drug Interaction Studies

Clinical Studies

Combined P-gp and Strong CYP3A Inducers:

Gilteritinib Cmax decreased approximately 30% and AUC decreased approximately 70% when co-administered with rifampin (a combined P-gp and strong CYP3A inducer).

Strong CYP3A Inhibitors:

Gilteritinib Cmax increased approximately 20% and AUC increased approximately 120% when co-administered with itraconazole (a strong CYP3A inhibitor).

Moderate CYP3A Inhibitors:

Gilteritinib Cmax increased approximately 16% and AUC increased approximately 40% when co-administered with fluconazole (a moderate CYP3A inhibitor).

CYP3A Substrates:

Midazolam (a CYP3A substrate) Cmax and AUC increased approximately 10% when co-administered with gilteritinib.

MATE1 Substrates:

Cephalexin (a MATE1 substrate) Cmax and AUC decreased by less than 10% when co-administered with gilteritinib.

In Vitro Studies

Gilteritinib inhibits human 5HT2B receptor or sigma nonspecific receptors, which may reduce the effects of drugs that target these receptors such as escitalopram, fluoxetine and sertraline.

Gilteritinib is a substrate of P-gp and BCRP. Gilteritinib inhibits BCRP, P-gp and OCT1 at clinically relevant concentrations.

13 NONCLINICAL TOXICOLOGY

13.1 Carcinogenesis, Mutagenesis, Impairment of Fertility

Carcinogenicity studies have not been performed with gilteritinib.

Gilteritinib was not mutagenic in a bacterial mutagenesis (Ames) assay and was not clastogenic in a chromosome aberration test assay in Chinese hamster lung cells. Gilteritinib was positive for the induction of micronuclei in mouse bone marrow cells from 65 mg/kg (195 mg/m^2) the mid dose tested (approximately 2.6 times the recommended human dose of 120 mg).

The effect of XOSPATA on human fertility is unknown. Administration of 10 mg/kg/day gilteritinib in the 4-week study in dogs (12 days of dosing) resulted in degeneration and necrosis of germ cells and spermatid giant cell formation in the testis as well as single cell necrosis of the epididymal duct epithelia of the epididymal head.

13.2 Animal Toxicology and/or Pharmacology

In the 13-week oral repeated dose toxicity studies in rats and dogs, target organs of toxicity included the eye and kidney.

14 CLINICAL STUDIES

14.1 Relapsed or Refractory Acute Myeloid Leukemia

The efficacy of XOSPATA was assessed in the ADMIRAL Trial (NCT02421939), which included adult patients with relapsed or refractory AML having a FLT3 ITD, D835, or I836 mutation by the LeukoStrat® CDx FLT3 Mutation Assay. XOSPATA was given orally at a starting dose of 120 mg daily until unacceptable toxicity or lack of clinical benefit.

First Interim Analysis

The efficacy of XOSPATA was established on the basis of the rate of complete remission (CR)/CR with partial hematological recovery (CRh), the duration of CR/CRh (DOR), and the rate of conversion from transfusion dependence to transfusion independence at the first interim analysis in the ADMIRAL trial (n=138). The median follow-up was 4.6 months (95% CI: 2.8, 15.8). Fourteen patients were still in remission at the time of the first interim DOR analysis. The efficacy results are shown in Table 5. For patients who achieved a CR/CRh, the median time to first response was 3.6 months (range, 0.9 to 9.6 months). The CR/CRh rate was 29 of 126 in patients with FLT3-ITD or FLT3-ITD/TKD and 0 of 12 in patients with FLT3-TKD only.

Among the 106 patients who were dependent on red blood cell (RBC) and/or platelet transfusions at baseline, 33 (31.1%) became independent of RBC and platelet transfusions during any 56-day post-baseline period. For the 32 patients who were independent of both RBC and platelet transfusions at baseline, 17 (53.1%) remained transfusion-independent during any 56-day post-baseline period.

Table 5: Efficacy Results in Patients with Relapsed or Refractory AML Treated with XOSPATA in the First Interim Analysis (ADMIRAL Trial)
Remission Rate | XOSPATA; N=138
CR [CR was defined as an absolute neutrophil count ≥1.0 x 10^9/L, platelets ≥100 x 10^9/L, normal marrow differential with <5% blasts, must have been red blood cells, platelet transfusion independent and no evidence of extramedullary leukemia.] /CRh [CRh was defined as marrow blasts <5%, partial hematologic recovery absolute neutrophil count ≥0.5 x 10^9/L and platelets ≥50 x 10^9/L, no evidence of extramedullary leukemia and could not have been classified as CR.] n/N (%) | 29/138 (21)
95% CI [The 95% CI rate was calculated using the exact method based on binomial distribution.] | 14.5, 28.8
Median DOR [DOR was defined as the time from the date of either first CR or CRh until the date of a documented relapse of any type. Deaths were counted as events.] (months) | 4.6
Range (months) | 0.1 to 15.8 [Response was ongoing.]
CR n/N (%) | 16/138 (11.6)
95% CI | 6.8, 18.1
Median DOR (months) | 8.6
Range (months) | 1 to 13.8
CRh n/N (%) | 13/138 (9.4)
95% CI | 5.1, 15.6
Median DOR (months) | 2.9
Range (months) | 0.1 to 15.8
CI: confidence interval; NE: not estimable; NR: not reached; Only responses prior to HSCT were included in response rate.

Final Analysis

The final analysis of the ADMIRAL trial included 371 adult patients randomized 2:1 to receive XOSPATA 120 mg once daily (n=247) over continuous 28-day cycles or a prespecified chemotherapy regimen (n=124). Randomization was stratified by response to first-line AML therapy and prespecified chemotherapy. The prespecified chemotherapy regimens included high intensity combinations (MEC and FLAG-IDA) and low intensity regimens (LDAC and AZA).

The demographic and disease characteristics of the randomized patients are shown in Table 6.

Table 6: Baseline Demographic and Disease Characteristics in Patients with Relapsed or Refractory AML in the Final Analysis (ADMIRAL Trial)
Demographic and Disease Characteristics | Xospata; (120 mg daily); N=247 | Chemotherapy; N=124
Demographics
Median Age (Years) (Range) | 62 (20, 84) | 62 (19, 85)
Age Categories, n (%)
<65 years | 141 (57) | 75 (60)
≥65 years | 106 (43) | 49 (40)
Sex, n (%)
Male | 116 (47) | 54 (44)
Female | 131 (53) | 70 (57)
Race, n (%)
White | 145 (59) | 75 (60)
Asian | 69 (28) | 33 (27)
Black or African American | 14 (6) | 7 (6)
Native Hawaiian or Other Pacific Islander | 1 (0.4) | 0
Other | 5 (2) | 1 (0.8)
Unknown/Missing | 13 (5) | 8 (6)
Baseline ECOG PS, n (%)
0-1 | 206 (83) | 105 (85)
≥2 | 41 (17) | 19 (15)
Disease Characteristics
Untreated relapse AML, n (%) | 151 (61) | 74 (60)
Primary refractory AML, n (%) | 96 (39) | 49 (40)
Refractory relapse AML, n (%) | 0 | 1 (0.8)
Number of Relapses, n (%)
0 | 96 (39) | 49 (40)
1 | 149 (60) | 74 (60)
2 or more | 2 (0.8) | 1 (0.8)
Median number of relapses (Range) | 1 (0, 2) | 1 (0, 2)
Transfusion Dependent at Baseline, n (%) [Patients were defined as transfusion dependent at baseline if they were dosed and received any red blood cell or platelet transfusions within the 56-day baseline period.] | 197 (80) | 97 (89)
FLT3 Mutation Status, n (%)
ITD alone | 215 (87) | 113 (91)
TKD alone | 21 (9) | 10 (8)
ITD and TKD | 7 (3) | 0
Prior Use of FLT3 Inhibitor [Prior use of FLT3 inhibitor is defined as “Yes” if patients received prior AML therapy of midostaurin, sorafenib or quizartinib; otherwise, prior use of FLT3 inhibitor was assigned as “No.”] , n (%)
No | 215 (87) | 110 (89)
Yes | 32 (13) | 14 (11)
Prespecified Chemotherapy
High Intensity | 149 (60) | 75 (60)
MEC [MEC: mitoxantrone 8 mg/m^2, etoposide 100 mg/m^2 and cytarabine 1000 mg/m^2 once daily by IV for 5 days] | - | 33 (27)
FLAG-IDA [FLAG-IDA: granulocyte colony-stimulating factor 300 mcg/m^2 once daily by SC days 1 to 5, fludarabine 30 mg/m^2 once daily by IV days 2 through 6, cytarabine 2000 mg/m^2 once daily by IV for days 2 through 6, idarubicin 10 mg/m^2 once daily by IV days 2 through 4] | - | 42 (34)
Low Intensity | 98 (40) | 49 (40)
LDAC [LDAC: cytarabine 20 mg twice daily by subcutaneous (SC) or intravenous (IV) for 10 days] | - | 17 (14)
AZA [AZA: azacitidine 75 mg/m^2 once daily by SC or IV for 7 days] | - | 32 (26)
AML: acute myeloid leukemia; FLT3: FMS-related tyrosine kinase 3; ITD: internal tandem duplication; TKD: D835/I836 tyrosine kinase domain point mutation; ECOG PS: Eastern Cooperative Oncology Group performance status

The final analysis included an assessment of OS, measured from the date of randomization until death by any cause. At the time of analysis, median follow-up was 17.8 months (range, 14.9 to 19.1). Patients randomized to the XOSPATA arm had significantly longer survival compared to the chemotherapy arm (HR 0.64; 95% CI: 0.49 – 0.83; 1-sided p-value: 0.0004). Figure 1 and Table 7 show the results of the OS analysis.

Exploratory subgroup analyses demonstrated that the hazard ratio for survival was 0.66 (95% CI: 0.47 – 0.93) for patients in the high intensity chemotherapy stratum and 0.56 (95% CI: 0.38 – 0.84) for patients in the low intensity chemotherapy stratum. The CR rates are shown in Table 7. For patients on XOSPATA and chemotherapy arms, the CR rates were 15.4% (95% CI: 10% – 22.3%) and 16% (95% CI: 8.6% – 26.3%), respectively, for patients in the high intensity chemotherapy stratum, and 12.2% (95% CI: 6.5% – 20.4%) and 2% (95% CI 0.1% – 10.9%), respectively, for patients in the low intensity chemotherapy stratum.

Table 7: OS and CR [CR was defined as an absolute neutrophil count ≥1.0 x 10^9/L, platelets ≥100 x 10^9/L, normal marrow differential with <5% blasts, must have been red blood cells, platelet transfusion independent and no evidence of extramedullary leukemia.] in Patients with Relapsed or Refractory AML in the Final Analysis (ADMIRAL Trial)
 | XOSPATA; N=247 | Chemotherapy; N=124
Overall Survival
Deaths, n (%) | 171 (69.2%) | 90 (72.6%)
Median in months (95% CI) | 9.3 (7.7, 10.7) | 5.6 (4.7, 7.3)
Hazard Ratio (95% CI) | 0.64 (0.49, 0.83)
p-value (1-sided) | 0.0004
Complete Remission
CR, n (%) | 35 (14.2%) | 13 (10.5%)
(95% CI [The 95% CI rate was calculated using the exact method based on binomial distribution.]) | (10.1, 19.2) | (5.7, 17.3)
Median DOR [DOR was defined as the time from the date of first remission until the date of a documented relapse.] (range) (months) | 14.8 (0.6 to 23.1+) | 1.8 (<0.1+ to 1.8)
CI: confidence interval; Only responses prior to HSCT were included in response rate.

Figure 1: Kaplan-Meier Plot of Overall Survival in ADMIRAL Trial

In the final analysis, the CR/CRh rate in the gilteritinib arm was 22.6% (55/243) and the DOR was 7.4 months (range, <0.1+ to 23.1+). For patients who achieved a CR/CRh, the median time to first response was 2 months (range, 0.9 to 9.6 months). The CR/CRh rate was 49 of 215 in patients with FLT3-ITD only, 3 of 7 in patients with FLT3-ITD/TKD and 3 of 21 in patients with FLT3-TKD only.

Among the 197 patients who were dependent on red blood cell (RBC) and/or platelet transfusions at baseline, 68 (34.5%) became independent of RBC and platelet transfusions during any 56-day post-baseline period. For the 49 patients who were independent of both RBC and platelet transfusions at baseline, 29 (59.2%) remained transfusion-independent during any 56-day post-baseline period

16 HOW SUPPLIED/STORAGE AND HANDLING

How Supplied

XOSPATA (gilteritinib) 40 mg tablets are supplied as light yellow, round-shaped, film-coated tablets debossed with the Astellas logo and ‘235’ on the same side. XOSPATA tablets are available in the following package size:

- Bottles of 90 tablets with Child Resistant Closure (NDC 0469-1425-90)

Storage

Store XOSPATA tablets at 20ºC to 25ºC (68°F to 77°F); excursions permitted between 15ºC to 30ºC (59°F to 86°F) [See USP Controlled Room Temperature]. Keep in original container until dispensed. Protect from light, moisture and humidity.

17 PATIENT COUNSELING INFORMATION

Advise the patient to read the FDA-approved patient labeling (Medication Guide).

Differentiation Syndrome

Advise patients of the risks of developing differentiation syndrome as early as 1 day after the start of therapy and during the first 3 months on treatment. Ask patients to immediately report any symptoms suggestive of differentiation syndrome, such as fever, cough or difficulty breathing, rash, low blood pressure, rapid weight gain, swelling of their arms or legs, or decreased urinary output, to their healthcare provider for further evaluation [see Boxed Warning and Warnings and Precautions (5.1)].

Posterior Reversible Encephalopathy Syndrome

Advise patients of the risk of developing posterior reversible encephalopathy syndrome (PRES). Ask patients to immediately report any symptoms suggestive of PRES, such as seizure and altered mental status, to their healthcare provider for further evaluation [see Warnings and Precautions (5.2)].

Prolonged QT Interval

Advise patients to consult their healthcare provider immediately if they feel faint, lose consciousness, or have signs or symptoms suggestive of arrhythmia. Advise patients with a history of hypokalemia or hypomagnesemia of the importance of monitoring their electrolytes [see Warnings and Precautions (5.3)].

Pancreatitis

Advise patients of the risk of pancreatitis and to contact their healthcare provider for signs or symptoms of pancreatitis, which include severe and persistent stomach pain, with or without nausea and vomiting [see Warnings and Precautions (5.4)].

Use of Contraceptives

- Advise female patients with reproductive potential to use effective contraceptive methods while receiving XOSPATA and for 6 months after completion of treatment.
- Advise patients to notify their healthcare provider immediately in the event of a pregnancy or if pregnancy is suspected during XOSPATA treatment.
- Advise males with female partners of reproductive potential to use effective contraception during treatment with XOSPATA and for 4 months after the last dose of XOSPATA [see Use in Specific Populations (8.3)].

Lactation

Advise women not to breastfeed during treatment with XOSPATA for 2 months after the last dose [see Use in Specific Populations (8.2)].

Dosing Instructions

- Advise patients not to break, crush or chew the tablets but to swallow them whole with a cup of water.
- Instruct patients that, if they miss a dose of XOSPATA, to take it as soon as possible on the same day, and at least 12 hours prior to the next scheduled dose, and return to the normal schedule the following day. Instruct patients to not take 2 doses within 12 hours [see Dosage and Administration (2.2)].

Distributed by:
Astellas Pharma US, Inc.
Northbrook, Illinois 60062

XOSPATA is a registered trademark of Astellas Pharma Inc.
LeukoStrat is a registered trademark of Invivoscribe, Inc.
©2021 Astellas Pharma US, Inc.
312959-GLT-USA

MEDICATION GUIDE
XOSPATA® (Zoh spah' tah)
(gilteritinib)
tablets

What is the most important information I should know about XOSPATA?

XOSPATA may cause serious side effects, including:

- Differentiation Syndrome. Differentiation syndrome is a condition that affects your blood cells and may be life-threatening or lead to death if not treated. Differentiation syndrome can happen as early as 1 day after starting XOSPATA and during the first 3 months of treatment. Call your healthcare provider or go to the nearest hospital emergency room right away if you develop any of the following symptoms of differentiation syndrome while taking XOSPATA:

- fever
- cough
- trouble breathing
- rash

- dizziness or lightheadedness
- rapid weight gain
- swelling of your arms or legs
- decreased urination

If you develop any of these symptoms of differentiation syndrome, your healthcare provider may treat you with a corticosteroid medicine and may monitor you in the hospital.

See “What are the possible side effects of XOSPATA?” for more information about side effects.

What is XOSPATA?
XOSPATA is a prescription medicine used to treat adults with acute myeloid leukemia (AML) who have a FMS-like tyrosine kinase 3 (FLT3) mutation:

- when the disease has come back, or
- has not improved after previous treatment(s).

Your healthcare provider will perform a test to make sure that XOSPATA is right for you.

It is not known if XOSPATA is safe and effective in children.

Do not take XOSPATA if you are allergic to gilteritinib or any of the ingredients in XOSPATA. See the end of this Medication Guide for a complete list of ingredients in XOSPATA.

Before taking XOSPATA, tell your healthcare provider about all of your medical conditions, including if you:

- have any heart problems, including a condition called long QT syndrome.
- have problems with abnormal electrolytes such as sodium, potassium, or magnesium levels.
- are pregnant or plan to become pregnant. XOSPATA can cause harm to your unborn baby. Tell your healthcare provider right away if you become pregnant or think you may be pregnant during treatment with XOSPATA.
  - If you are able to become pregnant, your healthcare provider may perform a pregnancy test 7 days before you start treatment with XOSPATA.
  - Females who are able to become pregnant should use effective birth control (contraception) during treatment with XOSPATA and for 6 months after the last dose of XOSPATA.
  - Males who have female partners that are able to become pregnant should use effective birth control (contraception) during treatment with XOSPATA and for 4 months after the last dose of XOSPATA.
- are breastfeeding or plan to breastfeed. It is not known if XOSPATA passes into your breast milk. Do not breastfeed during treatment with XOSPATA and for 2 months after the last dose of XOSPATA.

Tell your healthcare provider about all the medicines you take, including prescription and over-the-counter medicines, vitamins, and herbal supplements. XOSPATA may affect the way other medicines work and other medicines may affect how XOSPATA works.

How should I take XOSPATA?

- Take XOSPATA exactly as your healthcare provider tells you to. Do not change your dose or stop taking XOSPATA without talking to your healthcare provider.
- Take XOSPATA 1 time a day at about the same time each day.
- Swallow XOSPATA tablets whole. Do not break, crush, or chew the tablet.
- XOSPATA can be taken with or without food.

If you miss a dose of XOSPATA, or did not take it at the usual time, take your dose as soon as possible and at least 12 hours before your next dose. Return to your normal schedule the following day. Do not take 2 doses of XOSPATA within 12 hours.

What are the possible side effects of XOSPATA?
XOSPATA may cause serious side effects, including:

- See “What is the most important information I should know about XOSPATA?”
- Posterior Reversible Encephalopathy Syndrome (PRES). If you take XOSPATA, you may be at risk of developing a condition involving the brain called PRES. Tell your healthcare provider right away if you have a seizure or quickly worsening symptoms such as headache, decreased alertness, confusion, reduced eyesight, blurred vision, or other visual problems. Your healthcare provider will do a test to check for PRES. Your healthcare provider will stop XOSPATA if you develop PRES.
- Changes in the electrical activity of your heart called QTc prolongation. QTc prolongation can cause irregular heartbeats that can be life-threatening. Your healthcare provider will check the electrical activity of your heart with a test called an electrocardiogram (ECG) before you start taking XOSPATA and during your treatment with XOSPATA. Tell your healthcare provider right away if you feel dizzy, lightheaded, or faint. The risk of QT prolongation is higher in people with low blood magnesium or low blood potassium levels. Your healthcare provider will do blood tests to check your potassium and magnesium levels before and during your treatment with XOSPATA.
- Inflammation of the pancreas (pancreatitis). Tell your healthcare provider right away if you have severe stomach (abdomen) pain that does not go away. This pain may happen with or without nausea and vomiting.

The most common side effects of XOSPATA include:

- changes in liver function tests
- joint or muscle pain
- tiredness
- fever
- pain or sores in mouth or throat
- swelling of arms or legs

- rash
- diarrhea
- shortness of breath
- nausea
- cough
- constipation

- eye problems
- headache
- dizziness
- low blood pressure
- vomiting
- decreased urination

Your healthcare provider may tell you to decrease your dose, temporarily stop, or completely stop taking XOSPATA if you develop certain side effects during treatment with XOSPATA.

These are not all of the possible side effects of XOSPATA.

Call your doctor for medical advice about side effects. You may report side effects to FDA at 1-800-FDA-1088.

How should I store XOSPATA?

- XOSPATA comes in a child resistant package.
- Store XOSPATA at room temperature between 68°F to 77°F (20°C to 25°C).
- Keep XOSPATA in the original container to protect it from light, moisture, and humidity.
- Keep XOSPATA and all medicines out of the reach of children.

General information about the safe and effective use of XOSPATA.
Medicines are sometimes prescribed for purposes other than those listed in a Medication Guide. Do not use XOSPATA for a condition for which it was not prescribed. Do not give XOSPATA to other people, even if they have the same symptoms that you have. It may harm them. You can ask your pharmacist or healthcare provider for information about XOSPATA that is written for healthcare professionals.

What are the ingredients in XOSPATA?
Active ingredient: gilteritinib
Inactive ingredients: ferric oxide, hydroxypropyl cellulose, hypromellose, low-substituted hydroxypropyl cellulose, mannitol, magnesium stearate, polyethylene glycol, talc, and titanium dioxide.

Distributed by: Astellas Pharma US, Inc., Northbrook, Illinois 60062
XOSPATA is a registered trademark of Astellas Pharma Inc.
©2021 Astellas Pharma US, Inc.
For more information about XOSPATA, call 1-800-727-7003, or visit www.XOSPATA.com.
312959-GLT-USA

This Medication Guide has been approved by the U.S. Food and Drug Administration. Revised: Jan 2022

PACKAGE/LABEL PRINCIPAL DISPLAY PANEL – 40 mg Tablet Bottle Carton

NDC 0469-1425-90

XOSPATA®
(gilteritinib) tablets
40 mg
Do not break, crush or chew tablets.
90 tablets
Rx only